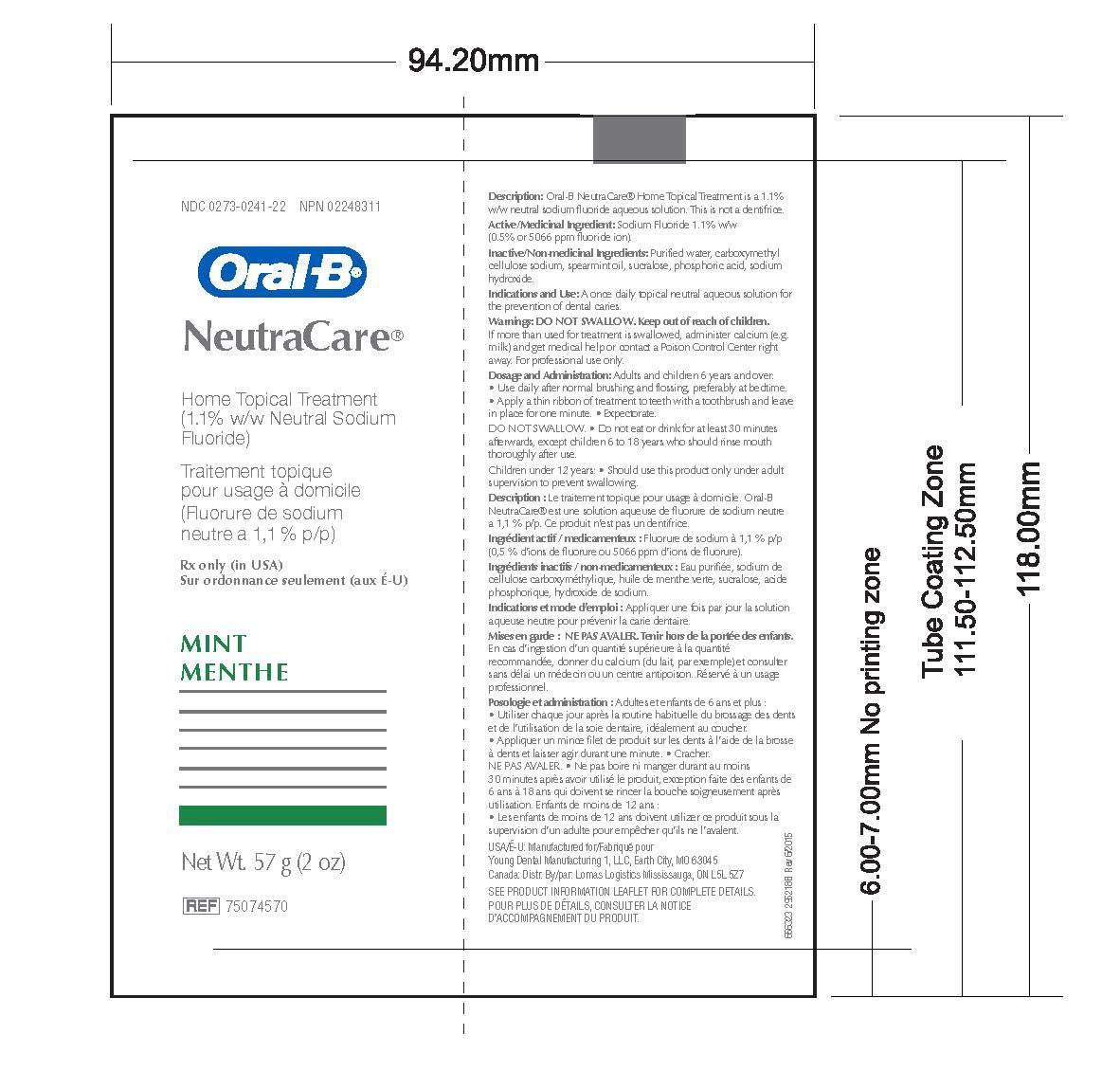 DRUG LABEL: Oral B NeutraCare 

NDC: 0273-0241 | Form: SOLUTION
Manufacturer: YOUNG DENTAL MANUFACTURING CO 1, LLC
Category: prescription | Type: HUMAN PRESCRIPTION DRUG LABEL
Date: 20230103

ACTIVE INGREDIENTS: SODIUM FLUORIDE 0.5 mg/1 g
INACTIVE INGREDIENTS: WATER; CARBOXYMETHYLCELLULOSE SODIUM; SPEARMINT OIL; SUCRALOSE; PHOSPHORIC ACID; SODIUM HYDROXIDE

Oral B NeutraCare

Inactives

Purified water, carboxymethylcellulose sodium, spearmint oil, sucralose, phosphoric acid,sodium hydroxide.

Indication and Usage

A once daily topical neutral aqueous solution for the prevention of dental caries.

After brushing with dentifrice, apply a thin ribbon of the formulation to teeth for at least1 minute using a toothbrush.Expectorate and do not eat, drink or rinse for at least 30 minutes.

Warnings

DO NOT SWALLOW. Keep outof reach of children.If more than used for treatment isswallowed, administer calcium(e.g. milk) and get medical help orcontact a Poison Control Centerright away. For professional use only.

Package Label

Product Label